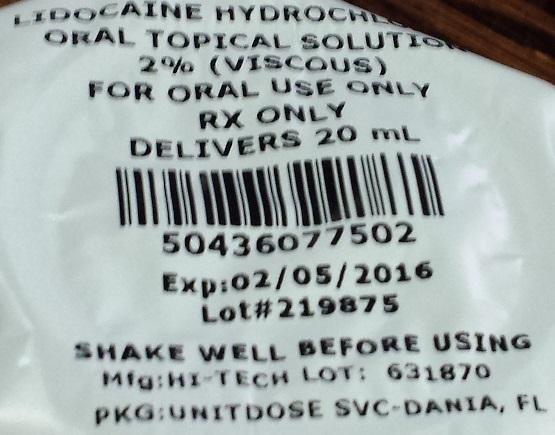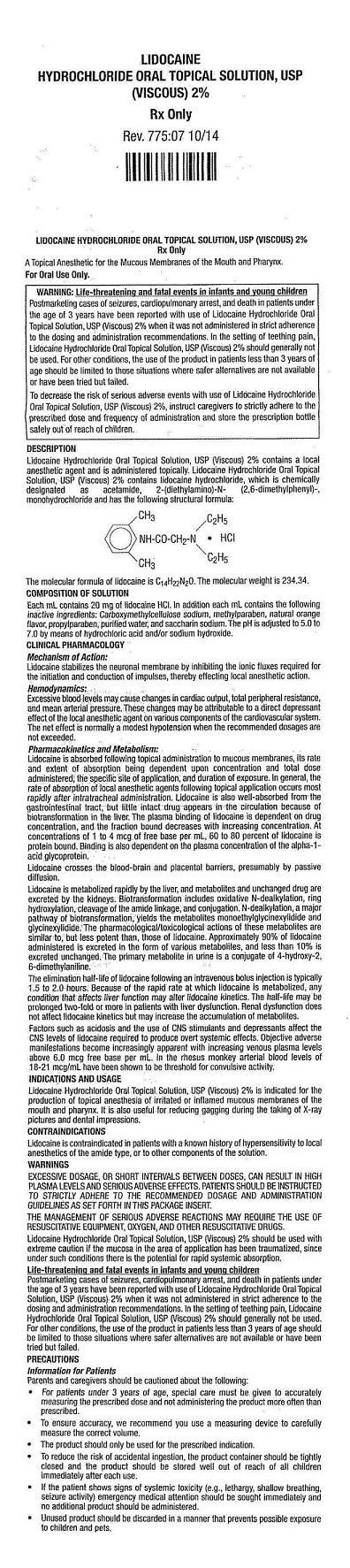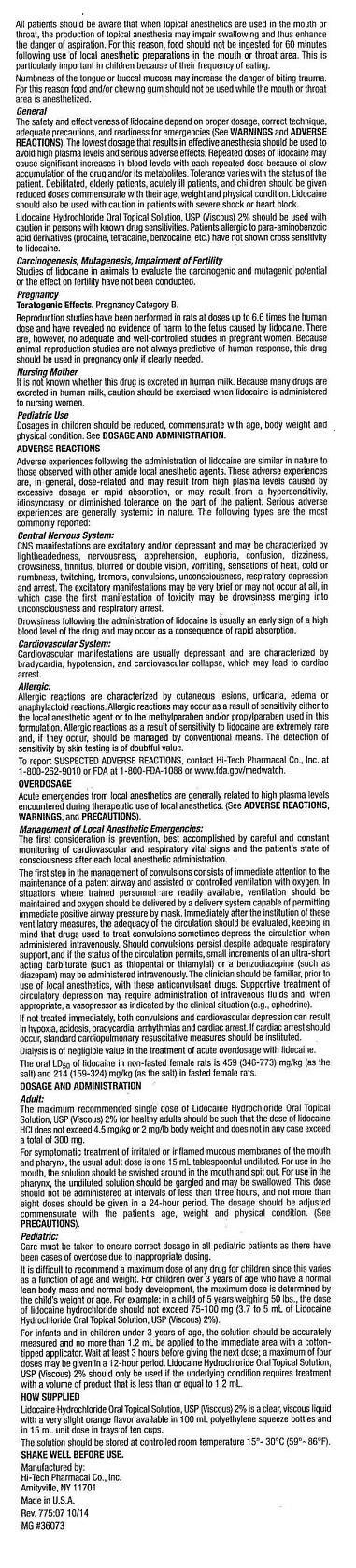 DRUG LABEL: LIDOCAINE HYDROCHLORIDE
NDC: 69938-101 | Form: GEL
Manufacturer: TRUE FIT RX LLC
Category: prescription | Type: HUMAN PRESCRIPTION DRUG LABEL
Date: 20150706

ACTIVE INGREDIENTS: LIDOCAINE 2 g/100 mL
INACTIVE INGREDIENTS: CARBOXYMETHYLCELLULOSE SODIUM; PROPYLPARABEN; WATER; SACCHARIN; ORANGE; SODIUM HYDROXIDE; HYDROCHLORIC ACID

DOSAGE AND ADMINISTRATION

DELIVERS 20 ML